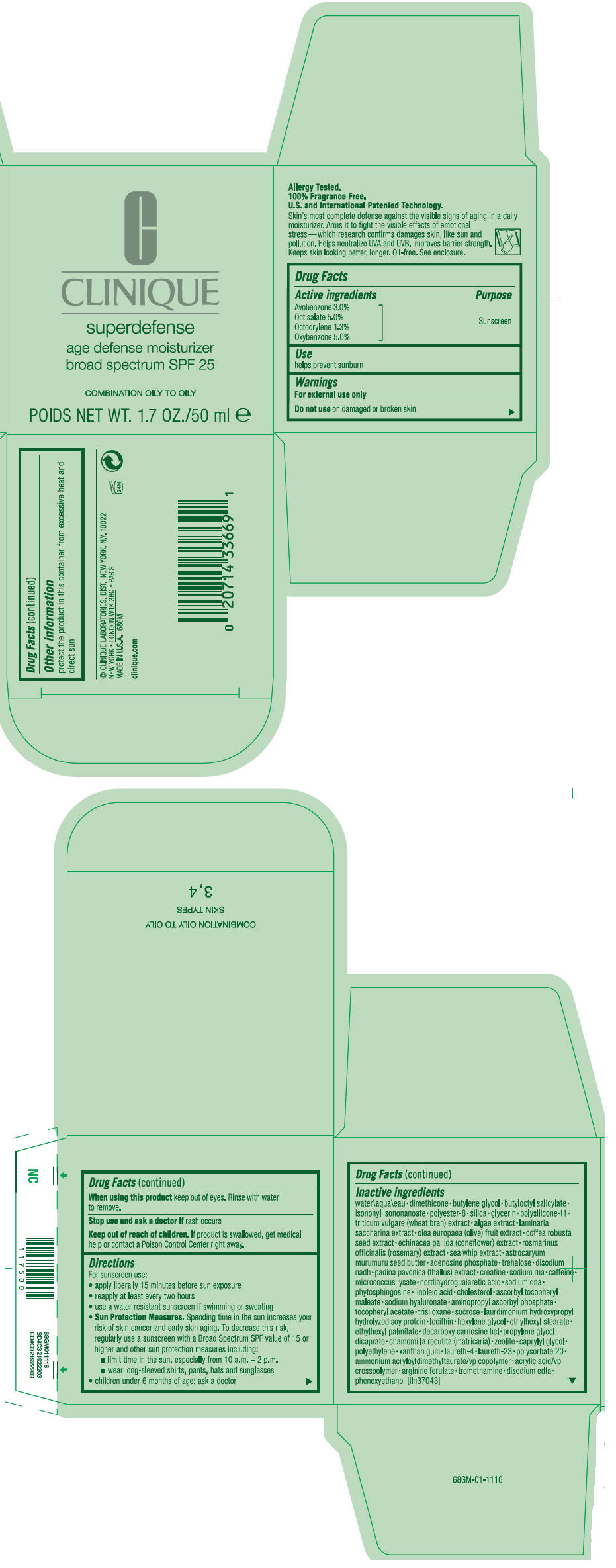 DRUG LABEL: CLINIQUE 
NDC: 49527-709 | Form: CREAM
Manufacturer: CLINIQUE LABORATORIES INC
Category: otc | Type: HUMAN OTC DRUG LABEL
Date: 20120305

ACTIVE INGREDIENTS: AVOBENZONE 3 mL/100 mL; OCTISALATE 5 mL/100 mL; OCTOCRYLENE 1.3 mL/100 mL; OXYBENZONE 5 mL/100 mL
INACTIVE INGREDIENTS: WATER; DIMETHICONE; BUTYLENE GLYCOL; BUTYLOCTYL SALICYLATE; ISONONYL ISONONANOATE; SILICON DIOXIDE; GLYCERIN; WHEAT BRAN; saccharina latissima thallus; BLACK OLIVE; ROBUSTA COFFEE BEAN; ECHINACEA PALLIDA; ROSEMARY; PSEUDOPTEROGORGIA ELISABETHAE; ASTROCARYUM MURUMURU SEED BUTTER; ADENOSINE PHOSPHATE; TREHALOSE; PADINA PAVONICA; CREATINE; CAFFEINE; MASOPROCOL; LINOLEIC ACID; CHOLESTEROL; HYALURONATE SODIUM; AMINOPROPYL ASCORBYL PHOSPHATE; .ALPHA.-TOCOPHEROL ACETATE; TRISILOXANE; SUCROSE; HEXYLENE GLYCOL; ETHYLHEXYL STEARATE; ETHYLHEXYL PALMITATE; PROPYLENE GLYCOL DICAPRATE; MATRICARIA RECUTITA; CAPRYLYL GLYCOL; HIGH DENSITY POLYETHYLENE; XANTHAN GUM; LAURETH-4; LAURETH-23; POLYSORBATE 20; AMMONIUM ACRYLOYLDIMETHYLTAURATE/VP COPOLYMER; TROMETHAMINE; EDETATE DISODIUM; PHENOXYETHANOL

CLINIQUE SUPERDEFENSE AGE DEFENSE MOISTURIZER BROAD SPECTRUM SPF 25 COMBINATION OILY TO OILY

Drug Facts

Active ingredients

Avobenzone 3.0%
Octisalate 5.0%
Octocrylene 1.3%
Oxybenzone 5.0%

Purpose

Sunscreen

Use

helps prevent sunburn

Warnings

For external use only

Do not use on damaged or broken skin

When using this product keep out of eyes. Rinse with water to remove.

Stop use and ask a doctor if rash occurs

Keep out of reach of children. If product is swallowed, get medical help or contact a Poison Control Center right away.

Directions

For sunscreen use:

- apply liberally 15 minutes before sun exposure
- reapply at least every two hours
- use a water resistant sunscreen if swimming or sweating
- Sun Protection Measures. Spending time in the sun increases your risk of skin cancer and early skin aging. To decrease this risk, regularly use a sunscreen with a Broad Spectrum SPF value of 15 or higher and other sun protection measures including:
  - limit time in the sun, especially from 10 a.m. – 2 p.m.
  - wear long-sleeved shirts, pants, hats and sunglasses
- children under 6 months of age: ask a doctor

Inactive ingredients

water • dimethicone • butylene glycol • butyloctyl salicylate • isononyl isononanoate • polyester-8 • silica • glycerin • polysilicone-11 • triticum vulgare (wheat bran) extract • algae extract • laminaria saccharina extract • olea europaea (olive) fruit extract • coffea robusta seed extract • echinacea pallida (coneflower) extract • rosmarinus officinalis (rosemary) extract • sea whip extract • astrocaryum murumuru seed butter • adenosine phosphate • trehalose • disodium nadh • padina pavonica (thallus) extract • creatine • sodium rna • caffeine • micrococcus lysate • nordihydroguaiaretic acid • sodium dna • phytosphingosine • linoleic acid • cholesterol • ascorbyl tocopheryl maleate • sodium hyaluronate • aminopropyl ascorbyl phosphate • tocopheryl acetate • trisiloxane • sucrose • laurdimonium hydroxypropyl hydrolyzed soy protein • lecithin • hexylene glycol • ethylhexyl stearate • ethylhexyl palmitate • decarboxy carnosine hcl • propylene glycol dicaprate • chamomilla recutita (matricaria) • zeolite • caprylyl glycol • polyethylene • xanthan gum • laureth-4 • laureth-23 • polysorbate 20 • ammonium acryloyldimethyltaurate/vp copolymer • acrylic acid/vp crosspolymer • arginine ferulate • tromethamine • disodium edta • phenoxyethanol [iln37043]

Other information

protect the product in this container from excessive heat and direct sun

© CLINIQUE LABORATORIES, DIST. NEW YORK, N.Y. 10022

PRINCIPAL DISPLAY PANEL - 50 ml Jar Carton

CLINIQUE

superdefense

age defense moisturizer
broad spectrum SPF 25

COMBINATION OILY TO OILY

POIDS NET WT. 1.7 OZ./50 ml e